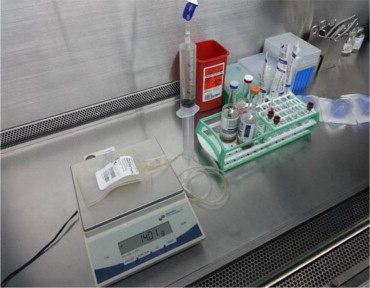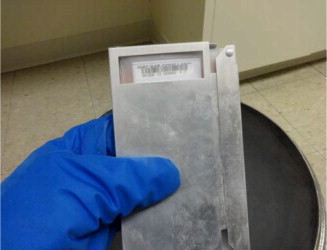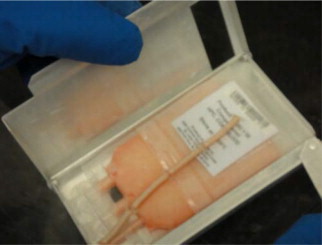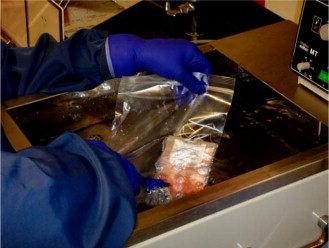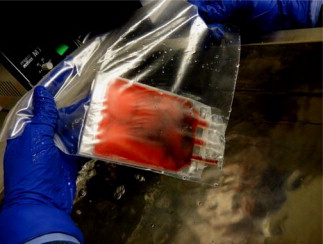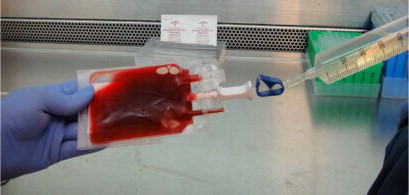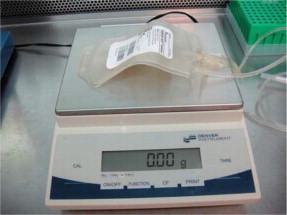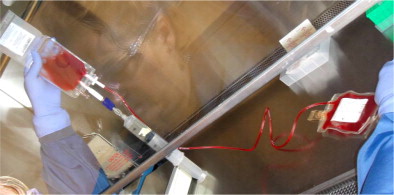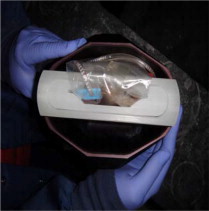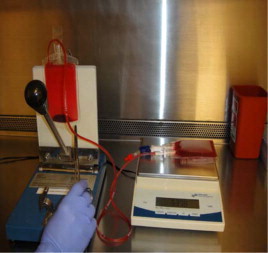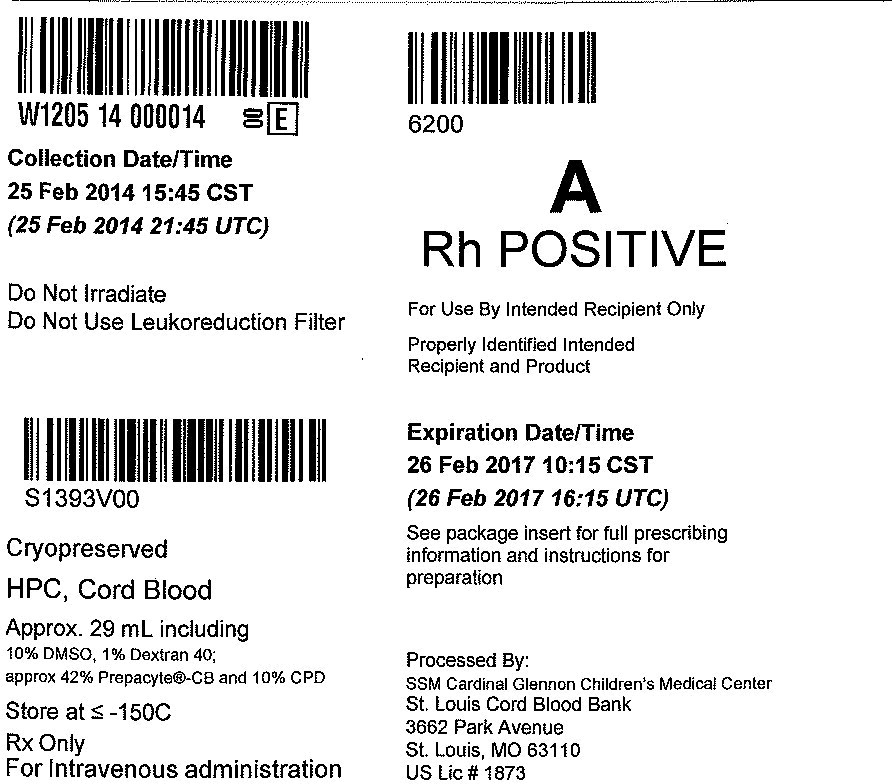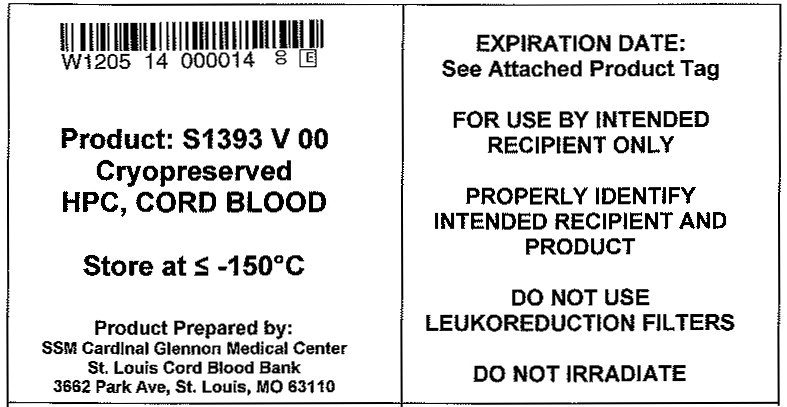 DRUG LABEL: ALLOCORD
NDC: W1205-S1393 | Form: INJECTION, SOLUTION
Manufacturer: SSM Cardinal Glennon Children's Medical Center St. Louis Cord Blood Bank
Category: other | Type: LICENSED MINIMALLY MANIPULATED CELLS LABEL
Date: 20180213

ACTIVE INGREDIENTS: Human Cord Blood Hematopoietic Progenitor Cell 500000000 1/35 mL
INACTIVE INGREDIENTS: Dimethyl Sulfoxide; Dextran 40

HIGHLIGHTS OF PRESCRIBING INFORMATION

These highlights do not include all the information needed to use ALLOCORD safely and effectively. See full prescribing information for ALLOCORD.
ALLOCORD (HPC, Cord Blood)
Injectable Suspension for Intravenous Use
Initial U.S. Approval: May 30, 2013

RECENT MAJOR CHANGES

Box Warning | 07/2015
Contraindications (4.0) | 07/2015

WARNING: FATAL INFUSION REACTIONS, GRAFT VERSUS HOST DISEASE, ENGRAFTMENT SYNDROME AND GRAFT FAILURE

See full prescribing information for complete boxed warning.

- Fatal infusion reactions: Monitor patients during infusion and discontinue for severe reactions. (5.1, 5.2).
- Graft-vs.-host disease (GVHD): GVHD may be fatal. Administration of immunosuppressive therapy may decrease the risk of GVHD (5.3).
- Engraftment syndrome: Engraftment syndrome may be fatal. Treat engraftment syndrome promptly with corticosteroids (5.4).
- Graft failure: Graft failure may be fatal. Monitor patients for laboratory evidence of hematopoietic recovery (5.5).

1 INDICATIONS AND USAGE

ALLOCORD,HPC, Cord Blood, is an allogeneic cord blood hematopoietic progenitor cell therapy indicated for use in unrelated donor hematopoietic progenitor cell transplantation procedures in conjunction with an appropriate preparative regimen for hematopoietic and immunologic reconstitution in patients with disorders affecting the hematopoietic system that are inherited, acquired, or result from myeloablative treatment (1).

The risk benefit assessment for an individual patient depends on the patient characteristics, including disease, stage, risk factors, and specific manifestations of the disease, on characteristics of the graft, and on other available treatments or types of hematopoietic progenitor cells (1).

2 DOSAGE AND ADMINISTRATION

- For intravenous use only
- Do not irradiate
- Unit selection and administration of ALLOCORD should be done under the direction of a physician experienced in hematopoietic progenitor cell transplantation (2).
- The recommended minimum dose is 2.5 x 10^7 nucleated cells/kg at cryopreservation (2.1).
- Do not administer ALLOCORD through the same tubing with other products except for normal saline (2.3).

3 DOSAGE FORMS AND STRENGTHS

Each unit contains a minimum of 5 x 10^8 total nucleated cells with at least 1.25 x 10^6 viable CD34+ cells at the time of cryopreservation. The exact pre-cryopreservation nucleated cell content of each unit is provided on the accompanying records (3).

4 CONTRAINDICATIONS

None

5 WARNINGS AND PRECAUTIONS

- Hypersensitivity Reactions (5.1)
- Infusion Reactions (5.2)
- Graft-versus-Host Disease (5.3)
- Engraftment Syndrome (5.4)
- Graft Failure (5.5)
- Malignancies of Donor Origin (5.6)
- Transmission of Serious Infections (5.7)
- Transmission of Rare Genetic Diseases (5.8)

6 ADVERSE REACTIONS

Mortality, from all causes, at 100 days post-transplant was 25% (5, 6.1).

The most common infusion-related adverse reactions (≥ 5%) are hypertension, vomiting, nausea, bradycardia, and fever (6.1).

To report SUSPECTED ADVERSE REACTIONS, contact the St. Louis Cord Blood Bank at 1-888-253-CORD (1-888-253-2673) and FDA at 1-800-FDA-1088 or www.fda.gov/medwatch

8 USE IN SPECIFIC POPULATIONS

Pregnancy: No animal or human data. Use only if clearly needed (8.1).

FULL PRESCRIBING INFORMATION

WARNING: FATAL INFUSION REACTIONS, GRAFT VERSUS HOST DISEASE, ENGRAFTMENT SYNDROME AND GRAFT FAILURE

Fatal infusion reactions: ALLOCORD administration can result in serious, including fatal, infusion reactions. Monitor patients and discontinue ALLOCORD infusion for severe reactions. [See Warnings and Precautions (5.1, 5.2)].

Graft-vs.-host disease (GVHD): GVHD is expected after administration of ALLOCORD, and may be fatal. Administration of immunosuppressive therapy may decrease the risk of GVHD [See Warnings and Precautions (5.3)].

Engraftment syndrome: Engraftment syndrome may progress to multi-organ failure and death. Treat engraftment syndrome promptly with corticosteroids [See Warnings and Precautions (5.4)].

Graft failure: Graft failure may be fatal. Monitor patients for laboratory evidence of hematopoietic recovery. Prior to choosing a specific unit of ALLOCORD, consider testing for HLA antibodies to identify patients who are alloimmunized [See Warnings and Precautions (5.5)].

1 INDICATIONS AND USAGE

ALLOCORD, HPC (Hematopoietic Progenitor Cell), Cord Blood, is an allogeneic cord blood hematopoietic progenitor cell therapy indicated for use in unrelated donor hematopoietic progenitor stem cell transplantation procedures in conjunction with an appropriate preparative regimen for hematopoietic and immunologic reconstitution in patients with disorders affecting the hematopoietic system that are inherited, acquired, or result from myeloablative treatment.

The risk benefit assessment for an individual patient depends on the patient characteristics, including disease, stage, risk factors, and specific manifestations of the disease, on characteristics of the graft, and on other available treatments or types of hematopoietic progenitor cells.

2 DOSAGE AND ADMINISTRATION

- For intravenous use only.
- Do not irradiate.

Unit selection and administration of ALLOCORD should be done under the direction of a physician experienced in hematopoietic progenitor cell transplantation.

2.1 Dosing

The recommended minimum dose is 2.5 x 10^7 nucleated cells/kg at cryopreservation. Multiple units may be required in order to achieve the appropriate dose.

Matching for at least 4 of 6 HLA-A antigens, HLA-B antigens, and HLA-DRB1 alleles is recommended. The HLA typing and nucleated cell content for each individual unit of ALLOCORD are documented in accompanying records.

2.2 Preparation for Infusion

ALLOCORD should be prepared by a trained healthcare professional.

- Do not irradiate ALLOCORD.
- See the appended detailed instructions for preparation of ALLOCORD for infusion.
- Once prepared for infusion, ALLOCORD may be stored at 4 to 25°C for up to 4 hours [see Instructions for Preparation for Infusion].
- The recommended limit on DMSO administration is 1 gram per kg body weight per day [see Warnings and Precautions (5.2) and Overdosage (10)].

2.3 Administration

ALLOCORD should be administered under the supervision of a qualified healthcare professional experienced in hematopoietic progenitor cell transplantation.

1. Confirm the identity of the patient for the specified unit of ALLOCORD prior to administration.
2. Confirm that emergency medications are available for use in the immediate area.
3. Ensure the patient is hydrated adequately.
4. Premedicate the patient 30 to 60 minutes before the administration of ALLOCORD. Premedication can include any or all of the following: antipyretics, histamine antagonists, and corticosteroids.
5. Inspect the product for any abnormalities such as unusual particulates and for breaches of container integrity prior to administration. Prior to infusion, discuss all such product irregularities with the laboratory issuing the product for infusion.
6. Administer ALLOCORD by intravenous infusion. Do not administer in the same tubing concurrently with products other than 0.9% Sodium Chloride, Injection (USP). ALLOCORD may be filtered through a 170 to 260 micron filter designed to remove clots. Do NOT use a filter designed to remove leukocytes.
7. For adults, begin infusion of ALLOCORD at 100 milliliters per hour and increase the rate as tolerated. For children, begin infusion of ALLOCORD at 1 milliliter per kg per hour and increase as tolerated. Reduce the infusion rate if the fluid load is not tolerated. Discontinue the infusion in the event of an allergic reaction or if the patient develops a moderate to severe infusion reaction [See Warnings and Precautions (5.2) and Adverse Reactions (6)].
8. Monitor the patient for adverse reactions during, and for at least six hours after, administration. Because ALLOCORD contains lysed red cells that may cause renal failure, careful monitoring of urine output is also recommended.

NOTE: If product is being prepared for a multi-unit infusion, infuse units independently. Should a reaction occur, appropriately manage the reaction before second unit is thawed for infusion.

3 DOSAGE FORMS AND STRENGTHS

Each unit of ALLOCORD contains a minimum of 5 x 10^8 total nucleated cells with a minimum of 1.25 x 10^6 viable CD34+ cells, suspended in 10% dimethyl sulfoxide (DMSO) and 1% Dextran 40, at the time of cryopreservation.

The exact pre-cryopreservation nucleated cell content is provided in accompanying records.

4 CONTRAINDICATIONS

None

5 WARNINGS AND PRECAUTIONS

5.1 Hypersensitivity Reactions

Allergic reactions may occur with infusion of HPC, Cord Blood, including ALLOCORD. Reactions include bronchospasm, wheezing, angioedema, pruritus and hives [see Adverse Reactions (6)]. Serious hypersensitivity reactions, including anaphylaxis, also have been reported. These reactions may be due to dimethyl sulfoxide (DMSO), Dextran 40, or a plasma component of ALLOCORD.

ALLOCORD may contain residual antibiotics if the cord blood donor was exposed to antibiotics in utero. Patients with a history of allergic reactions to antibiotics should be monitored for allergic reactions following ALLOCORD administration.

5.2 Infusion Reactions

Infusion reactions are expected to occur and include nausea, vomiting, fever, rigors or chills, flushing, dyspnea, hypoxemia, chest tightness, hypertension, tachycardia, bradycardia, dysgeusia, hematuria, and mild headache. Premedication with antipyretics, histamine antagonists, and corticosteroids may reduce the incidence and intensity of infusion reactions.

Severe reactions, including respiratory distress, severe bronchospasm, severe bradycardia with heart block or other arrhythmias, cardiac arrest, hypotension, hemolysis, elevated liver enzymes, renal compromise, encephalopathy, loss of consciousness, and seizure also may occur. Many of these reactions are related to the amount of DMSO administered. Minimizing the amount of DMSO administered may reduce the risk of such reactions, although idiosyncratic responses may occur even at DMSO doses thought to be tolerated. The actual amount of DMSO depends on the method of preparation of the product for infusion. Limiting the amount of DMSO infused to no more than 1 gram per kilogram per day is recommended [see Overdosage (10)].

Infusion reactions may begin within minutes of the start of infusion of ALLOCORD, although symptoms may continue to intensify and not peak for several hours after completion of the infusion. Monitor the patient closely during this period. If a reaction occurs, discontinue the infusion and institute supportive care as needed.

If infusing more than one unit of HPC, Cord Blood, on the same day, do not administer subsequent units until all signs and symptoms of infusion reactions from the prior unit have resolved.

5.3 Graft-versus-Host Disease

Acute and chronic graft-versus-host disease (GVHD) may occur in patients who have received ALLOCORD. Classic acute GVHD is manifested as fever, rash, elevated bilirubin and liver enzymes, and diarrhea. Patients transplanted with ALLOCORD also should receive immunosuppressive drugs to decrease the risk of GVHD [See Adverse Reactions (6.1)].

5.4 Engraftment Syndrome

Engraftment syndrome is manifested as unexplained fever and rash in the peri-engraftment period. Patients with engraftment syndrome also may have unexplained weight gain, hypoxemia, and pulmonary infiltrates in the absence of fluid overload or cardiac disease. If untreated, engraftment syndrome may progress to multi-organ failure and death. Begin treatment with corticosteroids once engraftment syndrome is recognized in order to ameliorate the symptoms [See Adverse Reactions (6.1)].

5.5 Graft Failure

Primary graft failure, which may be fatal, is defined as failure to achieve an absolute neutrophil count greater than 500 per microliter blood by Day 42 after transplantation. Immunologic rejection is the primary cause of graft failure. Patients should be monitored for laboratory evidence of hematopoietic recovery. Consider testing for HLA antibodies in order to identify patients who are alloimmunized prior to transplantation and to assist with choosing a unit with a suitable HLA type for the individual patient [See Adverse Reactions (6.1)].

5.6 Malignancies of Donor Origin

Patients who have undergone HPC, Cord Blood, transplantation may develop post-transplant lymphoproliferative disorder (PTLD), manifested as a lymphoma-like disease favoring non-nodal sites. PTLD is usually fatal if not treated.

The incidence of PTLD appears to be higher in patients who have received antithymocyte globulin. The etiology is thought to be donor lymphoid cells transformed by Epstein-Barr virus (EBV). Serial monitoring of blood for EBV DNA may be warranted in high-risk groups.

Leukemia of donor origin also has been reported in HPC, Cord Blood recipients. The natural history is presumed to be the same as that for de novo leukemia.

5.7 Transmission of Serious Infections

Transmission of infectious disease may occur because ALLOCORD is derived from human blood. Disease may be caused by known or unknown infectious agents. Donors are screened for increased risk of infection with human immunodeficiency virus (HIV), human T-cell lymphotropic virus (HTLV), hepatitis B virus (HBV), hepatitis C virus (HCV), T. pallidum, T. cruzi, West Nile Virus (WNV), transmissible spongiform encephalopathy (TSE) agents, and vaccinia. Donors are also screened for clinical evidence of sepsis, and communicable disease risks associated with xenotransplantation. Maternal blood samples are tested for HIV types 1 and 2, HTLV types I and II, HBV, HCV, T. pallidum, WNV, and T. cruzi. ALLOCORD is tested for sterility. These measures do not totally eliminate the risk of transmitting these or other transmissible infectious diseases and disease agents. Report the occurrence of a suspected transmitted infection to the St. Louis Cord Blood Bank of the SMM Cardinal Glennon Children's Medical Center at 1-888-253-CORD (1-888-253-2673).

Testing is also performed for evidence of donor infection due to cytomegalovirus (CMV). The result may be found in accompanying records.

5.8 Transmission of Rare Genetic Diseases

ALLOCORD may transmit rare genetic diseases involving the hematopoietic system for which donor screening and/or testing has not been performed [see Adverse Reactions (6.1)]. Cord blood donors have been screened by family history to exclude inherited disorders of the blood and marrow. ALLOCORD has been tested to exclude donors with sickle cell anemia, and anemias due to abnormalities in hemoglobins C, D, and E. Because of the age of the donor at the time ALLOCORD collection takes place, the ability to exclude rare genetic diseases is severely limited.

6 ADVERSE REACTIONS

Day-100 mortality from all causes was 25%.

The most common infusion-related adverse reactions (≥ 5%) are hypertension, vomiting, nausea, bradycardia, and fever.

6.1 Clinical Trials Experience

Because clinical trials are conducted under widely varying conditions, adverse reaction rates observed in the clinical trials of a drug cannot be directly compared to rates in the clinical trials of another drug and may not reflect the rates observed in practice.

The safety assessment of ALLOCORD is based primarily on review of the data submitted to the FDA dockets from various sources, the dataset for the COBLT Study, and published literature.

Infusion Reactions

The data described in Table 1 reflect exposure to 442 infusions of HPC, Cord Blood, (from multiple cord blood banks) in patients treated using a total nucleated cell dose ≥ 2.5 x 10^7/kg on a single-arm prospectivetrial or expanded access use (COBLT Study). The population was 59% male and the median age was 5 years (range 0.05-68 years), and included patients treated for hematologic malignancies, inherited metabolic disorders, primary immunodeficiencies, and bone marrow failure. Preparative regimens and graft-vs.-host disease prophylaxis were not standardized. The most common infusion reactions were hypertension, vomiting, nausea, and sinus bradycardia. Hypertension and any grades 3-4 infusion-related reactions occurred more frequently in patients receiving HPC, Cord Blood, in volumes greater than 150 milliliters and in pediatric patients. The rate of serious adverse cardiopulmonary reactions was 0.8%.

Table 1: Incidence of Infusion-Related Adverse Reactions Occurring in ≥1% of Infusions (COBLT Study)
 | Any grade | Grade 3-4
Any reaction | 65.4% | 27.6%
Hypertension | 48.0% | 21.3%
Vomiting | 14.5% | 0.2%
Nausea | 12.7% | 5.7%
Sinus bradycardia | 10.4% | 0
Fever | 5.2% | 0.2%
Sinus tachycardia | 4.5% | 0.2%
Allergy | 3.4% | 0.2%
Hypotension | 2.5% | 0
Hemoglobinuria | 2.1% | 0
Hypoxia | 2.0% | 2.0%

Information on infusion reactions was available from voluntary reports for 737 patients who received ALLOCORD. Preparative regimens and graft-vs.-host disease prophylaxis were not standardized. The reactions were not graded. An infusion reaction occurred in 13% of patients. The most common infusion reactions, occurring in ≥ 1% of patients, were hypertension (54%), vomiting (12%), dyspnea (9%), bradycardia (6%), nausea (4%), chest pain (2%), hemoglobinuria (2%), fever (2%) and hives (2%).

Other Adverse Reactions

For other adverse reactions, the raw clinical data from the dockets were pooled for 1299 (120 adult and 1179 pediatric) patients transplanted with HPC, Cord Blood, (from multiple cord blood banks) with total nucleated cell dose ≥ 2.5 x 10^7/kg. Of these, 66% (n=862) underwent transplantation as treatment for hematologic malignancy. The preparative regimens and graft-vs.-host disease prophylaxis varied. The median total nucleated cell dose was 6.4 x 10^7/kg (range, 2.5-73.8 x 10^7/kg). For these patients, Day-100 mortality from all causes was 25%. Primary graft failure occurred in 16%; 42% developed grades 2-4 acute graft-vs.-host disease; and 19% developed grades 3-4 acute graft-vs.-host disease.

Data from published literature and from observational registries, institutional databases, and cord blood bank reviews reported to the dockets for HPC, Cord Blood, (from multiple cord blood banks) revealed nine cases of donor cell leukemia, one case of transmission of infection, and one report of transplantation from a donor with an inheritable genetic disorder. The data are not sufficient to support reliable estimates of the incidences of these events.

In the COBLT Study, 15% of the patients developed engraftment syndrome.

8 USE IN SPECIFIC POPULATIONS

8.1 Pregnancy

Pregnancy Category C. Animal reproduction studies have not been conducted with ALLOCORD. It is also not known whether ALLOCORD can cause fetal harm when administered to a pregnant woman or can affect reproduction capacity. There are no adequate and well-controlled studies in pregnant women. ALLOCORD should be used during pregnancy only if the potential benefit justifies the potential risk to the fetus.

8.4 Pediatric Use

HPC, Cord Blood, has been used in pediatric patients with disorders affecting the hematopoietic system that are inherited, acquired, or resulted from myeloablative treatment [See Dosage and Administration (2), Adverse Reactions (6), and Clinical Studies (14)].

8.5 Geriatric Use

Clinical studies of HPC, Cord Blood, (from multiple cord blood banks) did not include sufficient numbers of subjects aged 65 years and over to determine whether they respond differently than younger subjects. In general, administration of ALLOCORD to patients over age 65 years should be cautious, reflecting their greater frequency of decreased hepatic, renal, or cardiac function, and of concomitant disease or other drug therapy.

8.6 Renal Disease

ALLOCORD contains Dextran 40 which is eliminated by the kidneys. The safety of ALLOCORD has not been established in patients with renal insufficiency or renal failure.

10 OVERDOSAGE

10.1 Human Overdosage Experience

There has been no experience with overdosage of HPC, Cord Blood, in human clinical trials. Single doses of ALLOCORD up to 67.0 x 10^7 TNC/kg have been administered. HPC, Cord Blood, prepared for infusion may contain dimethyl sulfoxide (DMSO). The maximum tolerated dose of DMSO has not been established, but it is customary not to exceed a DMSO dose of 1 gm/kg/day when given intravenously. Several cases of altered mental status and coma have been reported with higher doses of DMSO.

10.2 Management of Overdose

For DMSO overdosage, general supportive care is indicated. The role of other interventions to treat DMSO overdosage has not been established.

11 DESCRIPTION

ALLOCORD consists of hematopoietic progenitor cells, monocytes, lymphocytes, and granulocytes from human cord blood for intravenous infusion. Blood recovered from umbilical cord and placenta is volume reduced and partially depleted of red blood cells and plasma.

The active ingredient is hematopoietic progenitor cells which express the cell surface marker CD34. The potency of cord blood is determined by measuring the numbers of total nucleated cells (TNC) and CD34+ cells, and cell viability. Each unit of ALLOCORD contains a minimum of 5 x 10^8 total nucleated cells with at least 1.25 x 10^6 viable CD34+ cells at the time of cryopreservation. The cellular composition of ALLOCORD depends on the composition of cells in the blood recovered from the umbilical cord and placenta of the donor. The actual nucleated cell count, the CD34^+ cell count, the ABO group, and the HLA typing are listed in accompanying records sent with each individual unit.

ALLOCORD has the following inactive ingredients: PrepaCyte-CB separation solution, citrate-phosphate-dextrose, dimethyl sulfoxide (DMSO) and Dextran 40. When prepared for infusion according to instructions, the infusate contains the following inactive ingredients: PrepaCyte-CB separation solution, citrate-phosphate-dextrose, Dextran 40, human serum albumin, and residual DMSO.

12 CLINICAL PHARMACOLOGY

12.1 Mechanism of Action

Hematopoietic stem/progenitor cells from HPC, Cord Blood, migrate to the bone marrow where they divide and mature. The mature cells are released into the bloodstream, where some circulate and others migrate to tissue sites, partially or fully restoring blood counts and function, including immune function, of blood-borne cells of marrow origin [See Clinical Studies (14)].

In patients with enzymatic abnormalities due to certain severe types of storage disorders, mature leukocytes resulting from HPC, Cord Blood, transplantation may synthesize enzymes that may be able to circulate and improve cellular functions of some native tissues. However, the precise mechanism of action is unknown.

14 CLINICAL STUDIES

The effectiveness of HPC, Cord Blood, as defined by hematopoietic reconstitution, was demonstrated in one single-arm prospective study (COBLT Study), and in retrospective reviews of data from an observational database for ALLOCORD and data in the dockets and public information. Of the 1299 patients in the dockets and public data, 66% (n=862) underwent transplantation as treatment for hematologic malignancy. Results for patients who received a total nucleated cell dose ≥2.5 x 10^7/kg are shown in Table 2. Neutrophil recovery is defined as the time from transplantation to an absolute neutrophil count more than 500 per microliter. Platelet recovery is the time to a platelet count more than 20,000 per microliter. Erythrocyte recovery is the time to a reticulocyte count greater than 30,000 per microliter. The total nucleated cell dose and degree of HLA match were inversely associated with the time to neutrophil recovery in the docket data.

Table 2: Hematopoietic Recovery for Patients Transplanted with HPC, Cord Blood, Total Nucleated Cell (TNC) Dose ≥ 2.5 x 10^7/kg
Data Source | COBLT Study* | Docket* and Public Data* | ALLOCORD
Design | Single-arm prospective | Retrospective | Retrospective
Number of patients | 324 | 1299 | 1086
Median age (years) (range) | 4.6 (0.07 – 52.2) | 7.0 (<1 – 65.7) | 6.6 (0.05 – 70)
Gender | 59% male 41% female | 57% male 43% female | 54% male 43% female 3% unknown
Median TNC Dose (x 10^7/kg) (range) | 6.7 (2.6 – 38.8) | 6.4 (2.5 – 73.8) | 6.4 (2.5 – 67.0)
Neutrophil Recovery at Day 42 (95% CI) | 76% (71% – 81%) | 77% (75% – 79%) | 88%** (85% – 91%)
Platelet Recovery at Day 100 of 20,000/microliter (95% CI) | 57% (51% – 63%) | - | 87%** (83% – 91%)
Platelet Recovery at Day 100 of 50,000/microliter (95% CI) | 46% (39% – 51%) | 45% (42% – 48%) | 79%** (73% – 83%)
Erythrocyte Recovery at Day 100 (95% CI) | 65% (58% – 71%) | - | -
Median time to Neutrophil Recovery | 27 days | 25 days | 21 days**
Median time to Platelet Recovery of 20,000/microliter | 90 days | - | 48 days**
Median time to Platelet Recovery of 50,000/microliter | 113 days | 122 days | 56 days**
Median time to Erythrocyte Recovery | 64 days | - | -
* HPC, Cord Blood (from multiple cord blood banks)
** The analysis of hematopoietic recovery is based on a different number of patients, ranging from 335 to 442, for each variable because the amount of data missing is different for each variable.

16 HOW SUPPLIED/STORAGE AND HANDLING

ALLOCORD is supplied as a cryopreserved cell suspension in a sealed bag containing a minimum of 5 x 10^8 total nucleated cells with a minimum of 1.25 x 10^6 viable CD34+ cells in a volume of 35 milliliters (ISBT 128 Product Code S1393, ISBT 128 Facility Identifier Number W1205). The exact pre-cryopreservation nucleated cell content is provided in accompanying records.

Store ALLOCORD at or below -150 °C until ready for thawing and preparation.

17 PATIENT COUNSELING INFORMATION

Discuss the following with patients receiving ALLOCORD:

- Report immediately any signs and symptoms of acute infusion reactions, such as fever, chills, fatigue, breathing problems, dizziness, nausea, vomiting, headache, or muscle aches.
- Report immediately any signs or symptoms suggestive of graft-vs.-host disease, including rash, diarrhea, or yellowing of the eyes.

INSTRUCTIONS FOR PREPARATION FOR INFUSION

1 EQUIPMENT, REAGENTS, AND SUPPLIES

EQUIPMENT:

Biologic safety cabinet

Waterbath, 37°C

Heat sealer

Scale

Automated cell counter

Flow cytometer

Microscope

REAGENTS:

25% Albumin (Human), USP

Dextran 40 in Sodium Chloride Injection, USP or Dextran 40 in Dextrose Injection, USP

SUPPLIES:

Sterile sealable zip lock bag

Syringes - 1 mL, 3 mL, 5 mL, 30 mL, 60 mL

18 gauge safety needles

Blunt plastic cannulas

Sterile syringe caps (dual end: male/female)

Alcohol wipes

Plasma transfer sets (2 inch tubing, female luer adapter) – included with product shipment

Transfer packs – 150 mL, 300 mL

Blood culture vials

Blood culture device

Hemostat

2 mL cryovial

2 RECEIPT INSTRUCTIONS

ALLOCORD is shipped frozen in a steel canister that is contained in an insulating foam sleeve. ALLOCORD must be stored at or below -150 °C, either inside the container used for shipping (dry-shipper) or in a liquid nitrogen (LN2)-cooled storage device at the Transplant Center (recommended).

Upon receiving the shipment, perform the following steps:

1. Confirm receipt of the shipment and the identity of the expected unit.
2. Inspect the shipper for tampering or damage prior to opening.
3. Weigh the shipper and document the weight on the Unit Receipt Form.
4. Note the temperature displayed on the data logger and document the temperature on the Unit Receipt Form.
5. Using cryoprotective gloves, remove the product from the canister and place in a reservoir with LN2 or in the vapor phase of aLN2freezer.
6. Carefully open the cassette. Inspect the integrity of the unit(s) received and document its conditions on the Unit Receipt Form.
7. Confirm the identity of the cord blood unit. Include this check on the Unit Receipt Form.
8. Store the product in an LN2 storage vessel that maintains a temperature below -150°C.
9. Reserve the samples that accompany the unit as a DNA source for confirmatory testing or post engraftment studies:
  1. a segment remains on the unit; reserve it prior to thawing the unit
  2. an aliquot containing the material remaining from the red blood cell/plasma reduction
  3. an aliquot containing unmanipulated cord blood collected in Citrate Phosphate Dextrose (CPD)
  4. a spot card containing unmanipulated cord blood collected in CPD (in envelope)
  NOTE: Aside from the segment, ancillary samples are not intended to represent the cell count or potency of the cryopreserved product.
10. Replace data logger temperature probe wire inside the inner dry shipper container if necessary, and reassemble the shipper for return.
11. Fax the completed Unit Receipt Form to St. Louis Cord Blood Bank of the SSM Cardinal Glennon Children's Medical Center at 314-268-4186.
  NOTE: If there is any error or ambiguity with regard to the product documentation, close the canister and keep the product at LN2 temperature. Immediately advise the staff of the St. Louis Cord Blood Bank and the transplant physician. Do not proceed until the problem is resolved. If your LN2 storage tanks have no space to store the product in its canister and insulated sleeve, add LN2 to the St. Louis Cord Blood Bank dry-shipper to keep the product frozen until a completely satisfactory determination is made.

3 PREPARATION

1. Coordination with the clinical team
  1. Confirm the infusion time in advance, adjusting the start time for thaw so the unit is available for infusion when the recipient is ready.
  2. Consult with the clinicians about final product volume based on the recipient's weight and possible fluid restrictions.
2. General Information
  1. Use aseptic technique in a biological safety cabinet for all processing steps, including all open-container processing and all spiking of container ports.
  2. Use only sterile materials when processing the cellular product.
  3. Record the manufacturer information, lot number and expiration date (if applicable) of all reagents and disposables.
  4. Prepare the water bath and verify that the temperature is 37°C.
3. Prepare the reconstitution solution
  1. Combine 250 mL Dextran 40 and 50 mL 25% albumin in a 300 mL transfer pack. Clamp the tubing with a hemostat.
  2. Using appropriate sized syringes, withdraw the following and cap the syringes with blunt plastic cannula:
    1. 50 mL of reconstitution solution. If the total frozen volume (product + DMSO volume) exceeds the standard 50mL reconstitution solution, use a volume of reconstitution solution equal to the total frozen volume so the dilution ratio is at least 1:1
    2. 30 mL of reconstitution solution to be used as a container rinse for microbial culturing
4. Obtain product
  1. Prepare a portable canister with LN2 using appropriate personal protective equipment (gloves, gowns, face shield).
  2. Product verification requires two members of the laboratory staff. With product and recipient files at hand, locate and remove the product from its location in the freezer, but maintaining in vapor phase. Expeditiously verify product identity, labeling, accuracy of information, and container integrity.
  3. Remove any segment attached to the unit, place into a 2 mL cryovial and store in either vapor or liquid phase of nitrogen (<-150°C).
  4. Immediately transfer the product from LN2 storage tank into the portable canister containing LN2.

4 PROCEDURE

Reconstitution or simple dilution of ALLOCORD with dextran/human serum albumin (HSA) solution, using the Thawing and Diluting procedures described below, is recommended. The Alternate Procedure – Washing may be considered if the infusion volume and/or DMSO dose are contraindicated (>1 mL/kg).

NOTE: Minimize the time from initiation of thaw to completion of infusion.

THAWING:

1. Verify the identity of the product being thawed.
2. Remove the ALLOCORD unit from the cassette. Examine the cryobag for breaks or cracks.
3. Carefully place the unit inside a sterile sealable zip-lock bag, and submerge in the 37°C water bath, keeping port(s) dry and above water.
4. Document the thaw start time.
5. To accelerate thawing, gently knead contents of bag.
  NOTE: Inspect for leaks! If container integrity is observed to be compromised, position the cryobag and/or clamp with hemostats to prevent further escape of blood.
6. When the contents of the cryobag become slushy, remove the bag from the 37ºC water bath.
7. Note the thaw stop time. Product expiration time is four hours from this step.
8. Gently wipe the outside surface of the cryobag with alcohol, and place the cryobag into the biologic safety cabinet.
  DILUTING:
9. Insert a plasma transfer set into the cryobag.
10. Attach the syringe containing the 50mL reconstitution solution to the transfer set on the cryobag.
11. Slowly introduce approximately half the volume of the reconstitution solution to the thawed product while mixing the fluids in the bag.
12. Insert the spike of a correctly labeled appropriate volume capacity transfer pack into the second access port of the cryobag.
13. Weigh the empty transfer pack to determine the tare weight of the bag.
14. Drain the contents from the cryobag into transfer pack.
15. Clamp the tubing between the bags with a hemostat.
16. Add the remaining reconstitution solution to the cryobag.
17. Mix well to rinse the cells from the bag and drain into transfer pack.
18. Clamp the tubing between the bags.
19. Weigh the transfer pack subtracting the tare weight to get product volume.
20. Insert a transfer set into the product transfer pack.
21. Aseptically attach a 3 mL syringe and aspirate a 1 mL aliquot for quality control testing.
22. Deliver the 1mL testing aliquot into a labeled aliquot tube.
23. Subtract the 1mL (testing aliquot) from product volume to determine infusion volume. Record the infusion volume which will be used for calculating cell numbers.
24. Heat seal the tubing between the cryobag and the transfer pack.
25. Cut tubing at the seals and separate the bags.
  NOTE: At this point, it is approximately 30 minutes from infusion. Notify the clinical transplant team to pre-medicate the patient as ordered.
26. Aseptically introduce the 30 mL of reconstitution solution from the syringe prepared in step 3.c.ii.2) into the (now empty) original product cryobag.
27. Immediately transport the product to the clinical transplant site per the facility's SOP.

ALTERNATIVE PROCEDURE - WASHING:

Perform steps a. through r. of the Thawing Procedure and Diluting Procedure as outlined above, then complete the following:

1. Place the transfer pack into a sterile overwrap bag ready for centrifugation.
2. Support bag in centrifuge bucket insert to prevent the formation of creases during centrifugation.
3. Balance carriers and centrifuge at 650 x g (1500 rpm) for 20 minutes at 10°C (no brake).
4. Carefully remove the transfer pack from the centrifuge into the biologic safety cabinet, placing the transfer pack into a plasma expresser.
5. Using the original cryobag to collect the waste volume, express 75% of the volume of reconstitution solution originally added to the thawed product pre-centrifugation. Avoid accidental passage of cells with the supernatant.
6. Allow the cells to rest for five minutes. Resuspend the sedimented cell pellet by gentle agitation.
7. Obtain quality control samples as described in steps s. through aa. above.

5 QUALITY CONTROL:

Perform quality control assays per transplant center policies and procedures using the aliquot of thawed product obtained in step u above. Recommended assays include:

1. Nucleated Cell count
2. Viability test
3. Viable CD34+ cell count
4. Colony Forming Unit
5. Microbial cultures (aerobic, anaerobic and fungal)

CALCULATIONS:

Infusion TNC [x10^9] = (WBC/mL + NRBC/mL [x10^6]) x infusion volume (mL)

TNC dose [x10^7/kg] = Infusion TNC [x10^9]
Recipient wt (kg)

Post-thaw TNC recovery [%] = TNC of thawed product [x10^9] x 100
TNC of original frozen product [x10^9]

Total CD34+ cells [x10^6] = CD34+ cells/mL x dilution factor x 1000 mL x product volume (mL)

CD34+ cell dose [x10^5/kg] = Absolute CD34+ cell cells (x10^6) ÷ Recipient weight (kg)

Product RBC volume [mL] = product hematocrit x product volume (mL)

RBC dose [mL/kg] = Product RBC volume [mL] ÷ Recipient weight (kg)

Product CFU count [x10^5] = Colonies scored per 10^5 NC x product TNC [x10^9]
10^5

CFU dose [x10^4/kg] = Product CFU count [x10^5] ÷ Recipient weight (kg)

6 CONTACT INFORMATION

SSM Cardinal Glennon Children's Medical Center
St. Louis Cord Blood Bank (SLCBB)
3662 Park Avenue
St. Louis, MO 63110

SLCBB Hours: Monday-Friday, 7:00am – 5:00pm, Central Time
SLCBB Phone Number: 314-268-2787 or 888-453-CORD (888-453-2673)
SLCBB Fax Number: 314-268-4186

After Hours Numbers:
Director: 314-486-2488
Distribution: 314-277-1638

DISTRIBUTED BY:
SSM Cardinal Glennon Children's Medical Center
dba St. Louis Cord Blood Bank
1465 South Grand Blvd
St. Louis, MO 63104
US License 1873

Principal Display Panel - Canister Label

6200

A
Rh POSITIVE

For Use By Intended Recipient Only

Properly Identified Intended
Recipient and Product

Expiration Date/Time

26 Feb 2017 10:15 CST
(26 Feb 2014 16:15 UTC)

See package insert for full prescribing
information and instructions for
preparation

Processed By:

SSM Cardinal Glennon Children's Medical Center
St. Louis Cord Blood Bank

3662 Park Avenue
St. Louis, MO 63110

US Lic# 1873

"W1205 14 000014"

Collection Date/Time

25 Feb 2014 15:45 CST
(25 Feb 2014 21:45 UTC)

Do Not Irradiate

Do Not Use Leukoreduction Filter

S1393V00

Cryopreserved

HPC, Cord Blood

Approx. 29 mL including

10% DMSO, 1% Dextran 40;
approx 42% Prepacyte®-CB and 10% CPD

Store at ≤ -150C

Rx Only

For Intravenous administration

Principal Display Panel - Bag Label

"W1205 14 000014"

Product: S1393 V 00
Cryopreserved
HPC, CORD BLOOD

Store at ≤ -150°C

Product Prepared by:

SSM Cardinal Glennon Children's Medical Center
St. Louis Cord Blood Bank

3662 Park Avenue, St. Louis, MO 63110

EXPIRATION DATE:

See Attached Product Tag

FOR USE BY INTENDED
RECIPIENT ONLY

PROPERLY IDENTIFY
INTENDED RECIPIENT AND
PRODUCT

DO NOT USE
LEUKOREDUCTION FILTERS

DO NOT IRRADIATE